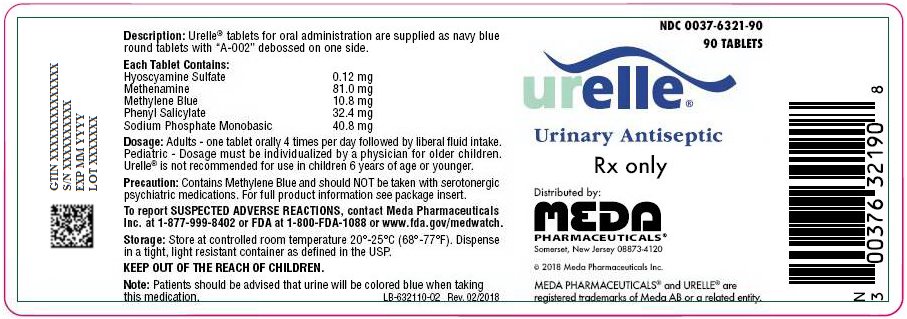 DRUG LABEL: URELLE
NDC: 0037-6321 | Form: TABLET
Manufacturer: Viatris Specialty LLC
Category: prescription | Type: HUMAN PRESCRIPTION DRUG LABEL
Date: 20150113

ACTIVE INGREDIENTS: HYOSCYAMINE SULFATE 0.12 mg/1 1; METHENAMINE 81 mg/1 1; METHYLENE BLUE 10.8 mg/1 1; PHENYL SALICYLATE 32.4 mg/1 1; SODIUM PHOSPHATE, MONOBASIC, MONOHYDRATE 40.8 mg/1 1
INACTIVE INGREDIENTS: STARCH, CORN; ANHYDROUS DIBASIC CALCIUM PHOSPHATE; FD&C BLUE NO. 2; MAGNESIUM STEARATE; MICROCRYSTALLINE CELLULOSE; POLYETHYLENE GLYCOL, UNSPECIFIED; POLYVINYL ALCOHOL, UNSPECIFIED; TALC; TITANIUM DIOXIDE

URELLE®
Urinary Antiseptic

DESCRIPTION:

Urelle® tablets for oral administration are supplied as navy blue round tablets with “A-002” debossed on one side.

Each Tablet Contains:

Hyoscyamine Sulfate 0.12 mg

Methenamine 81.0 mg

Methylene Blue 10.8 mg

Phenyl Salicylate 32.4 mg

Sodium Phosphate Monobasic 40.8 mg

INACTIVE INGREDIENTS:

Corn Starch, Dicalcium Phosphate, FD&C Blue #2/Indigo Carmine Aluminum Lake, Magnesium Stearate, Microcrystalline Cellulose, Polyethylene Glycol, Polyvinyl Alcohol, Talc, Titanium Dioxide.

INDICATIONS and USAGE:

Urelle® is indicated for the treatment of symptoms of irritative voiding. Indicated for the relief of local symptoms, such as inflammation, hypermotility, and pain, which accompany lower urinary tract infections. Indicated for the relief of urinary tract symptoms caused by diagnostic procedures.

CONTRAINDICATIONS:

Hypersensitivity to any of the ingredients is possible. Risk - benefit should be carefully considered when the following medical problems exist: cardiac disease (especially cardiac arrhythmias, congestive heart failure, coronary heart disease, mitral stenosis); gastrointestinal tract obstructive disease; glaucoma; myasthenia gravis; acute urinary retention may be precipitated in obstructive uropathy (such as bladder neck obstruction due to prostatic hypertrophy).

WARNINGS:

If rapid pulse, dizziness, or blurring of vision occurs, discontinue use immediately.

Patients should be advised that urine will be colored blue when taking this medication. Do not exceed recommended dosage.

PRECAUTIONS:

Cross sensitivity and/or related problems - patients intolerant of belladonna alkaloids or salicylates may be intolerant of this medication also. Delay in gastric emptying could complicate the management of gastric ulcers.

Urelle® contains methylene blue. Methylene blue should generally NOT be given to patients taking serotonergic drugs.

Drug Interactions:

Although the exact mechanism of this drug interaction is unknown, methylene blue inhibits the action of monoamine oxidase A— an enzyme responsible for breaking down serotonin in the brain. It is believed that when methylene blue is given to patients taking serotonergic psychiatric medications, high levels of serotonin can build up in the brain, causing toxicity. This is referred to as Serotonin Syndrome. Signs and symptoms of Serotonin Syndrome include mental changes (confusion, hyperactivity, memory problems), muscle twitching, excessive sweating, shivering or shaking, diarrhea, trouble with coordination, and/or fever.

Additional Information for Healthcare Professionals:

Methylene blue can interact with serotonergic psychiatric medications and cause serious CNS toxicity.

In emergency situations requiring life-threatening or urgent treatment with methylene blue (as described above), the availability of alternative interventions should be considered and the benefit of methylene blue treatment should be weighed against the risk of serotonin toxicity. If methylene blue must be administered to a patient receiving a serotonergic drug, the serotonergic drug must be immediately stopped, and the patient should be closely monitored for emergent symptoms of CNS toxicity for two weeks (five weeks if fluoxetine [Prozac] was taken), or until 24 hours after the last dose of methylene blue, whichever comes first.

In non-emergency situations when non-urgent treatment with methylene blue is contemplated and planned, the serotonergic psychiatric medication should be stopped to allow its activity in the brain to dissipate. Most serotonergic psychiatric drugs should be stopped at least 2 weeks in advance of methylene blue treatment. Fluoxetine (Prozac), which has a longer half-life compared to similar drugs, should be stopped at least 5 weeks in advance.

Treatment with the serotonergic psychiatric medication may be resumed 24 hours after the last dose of methylene blue.

Serotonergic psychiatric medications should not be started in a patient receiving methylene blue. Wait until 24 hours after the last dose of methylene blue before starting the antidepressant.

Educate your patients to recognize the symptoms of serotonin toxicity or CNS toxicity and advise them to contact a healthcare professional immediately if they experience any symptoms while taking serotonergic psychiatric medications or methylene blue.

ADVERSE REACTIONS

To report SUSPECTED ADVERSE REACTIONS, contact Meda Pharmaceuticals Inc. at 1-877-999-8402 or FDA at 1-800-FDA-1088 or www.fda.gov/medwatch.

DOSAGE and ADMINISTRATION:

Adults – One tablet orally 4 times per day followed by liberal fluid intake.

Pediatric – Dosage must be individualized by a physician for older children. Urelle® is not recommended for use in children 6 years of age or younger.

HOW SUPPLIED:

Urelle® tablets for oral administration are supplied in child resistant bottles of 90 tablets (NDC 0037-6321-90).

STORAGE AND HANDLING

Store at controlled room temperature 20°-25°C (68°-77°F).

Dispense in a tight, light resistant container as defined in the USP.

KEEP THIS AND ALL DRUGS OUT OF THE REACH OF CHILDREN.

Distributed by:
Meda Pharmaceuticals®
Somerset, New Jersey 08873-4120

© 2014 Meda Pharmaceuticals Inc.

MEDA PHARMACEUTICALS and URELLE are registered trademarks of Meda AB or a related entity.

Rx Only

IN-632110-01

Rev. 07/2014

PRINCIPAL DISPLAY PANEL – BOTTLE LABEL

NDC 0037-6321-90
90 TABLETS

Urelle®
Urinary Antiseptic

Rx only

Distributed by:
MEDA
PHARMACEUTICALS®
Somerset, New Jersey 08873-4120

© 2018 Meda Pharmaceuticals Inc.

MEDA PHARMACEUTICALS® and URELLE® are
registered trademarks of Meda AB or a related entity.

Description: Urelle® tablets for oral administration are supplied as navy blue
round tablets with “A-002” debossed on one side.

Each Tablet Contains:
Hyoscyamine Sulfate 0.12 mg
Methenamine 81.0 mg
Methylene Blue 10.8 mg
Phenyl Salicylate 32.4 mg
Sodium Phosphate Monobasic 40.8 mg

Dosage: Adults - one tablet orally 4 times per day followed by liberal fluid intake.
Pediatric - Dosage must be individualized by a physician for older children.
Urelle® is not recommended for use in children 6 years of age or younger.

Precaution: Contains Methylene Blue and should NOT be taken with serotonergic
psychiatric medications. For full product information see package insert.

To report SUSPECTED ADVERSE REACTIONS, contact Meda Pharmaceuticals
Inc. at 1-877-999-8402 or FDA at 1-800-FDA-1088 or www.fda.gov/medwatch.

Storage: Store at controlled room temperature 20°-25°C (68°-77°F). Dispense
in a tight, light resistant container as defined in the USP.

KEEP OUT OF THE REACH OF CHILDREN.

Note: Patients should be advised that urine will be colored blue when taking
this medication.

LB-632110-02 Rev. 02/2018